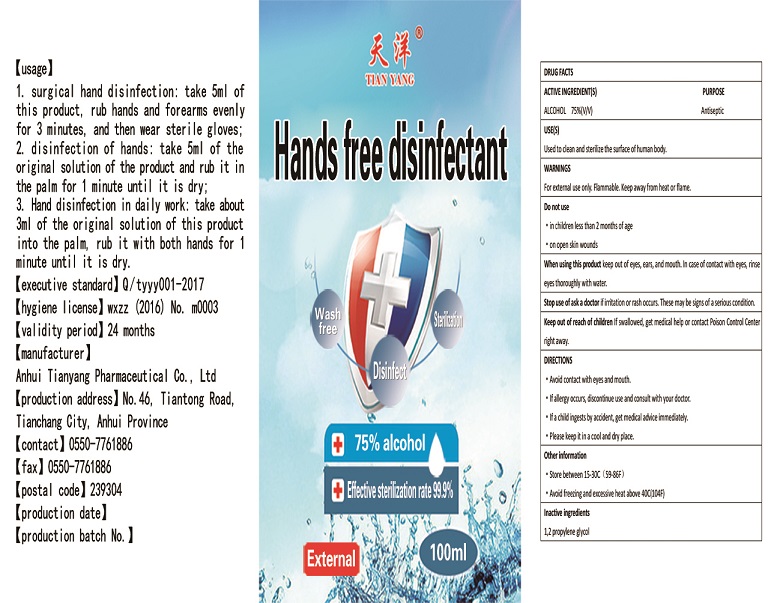 DRUG LABEL: Hands free disinfectant
NDC: 52983-002 | Form: SOLUTION
Manufacturer: Anhui Tianyang Pharmaceutical Co., Ltd.
Category: otc | Type: HUMAN OTC DRUG LABEL
Date: 20201224

ACTIVE INGREDIENTS: ALCOHOL 75 mL/100 mL
INACTIVE INGREDIENTS: PROPYLENE GLYCOL; WATER

Active Ingredient(s)

Alcohol 75% v/v. Purpose: Antiseptic

Purpose

Antiseptic

Use

Used to clean and sterilize the surface of human body.

Warnings

For external use only. Flammable. Keep away from heat or flame

Do not use

- in children less than 2 months of age
- on open skin wounds

When using this product keep out of eyes, ears, and mouth. In case of contact with eyes, rinse eyes thoroughly with water.
Stop use and ask a doctor if irritation or rash occurs. These may be signs of a serious condition.
Keep out of reach of children. If swallowed, get medical help or contact a Poison Control Center right away.

Stop use and ask a doctor if irritation or rash occurs. These may be signs of a serious condition.

Keep out of reach of children. If swallowed, get medical help or contact a Poison Control Center right away.

Directions

Avoid contact with eyes and mouth.

If allergy occurs,discontinue use and consult with your doctor.

If a child ingests by accident,get medical advice immediately.

Please keep it in a cool and dry place

Other information

- Store between 15-30C (59-86F)
- Avoid freezing and excessive heat above 40C (104F)

Inactive ingredients

1,2 propylene glycol,water